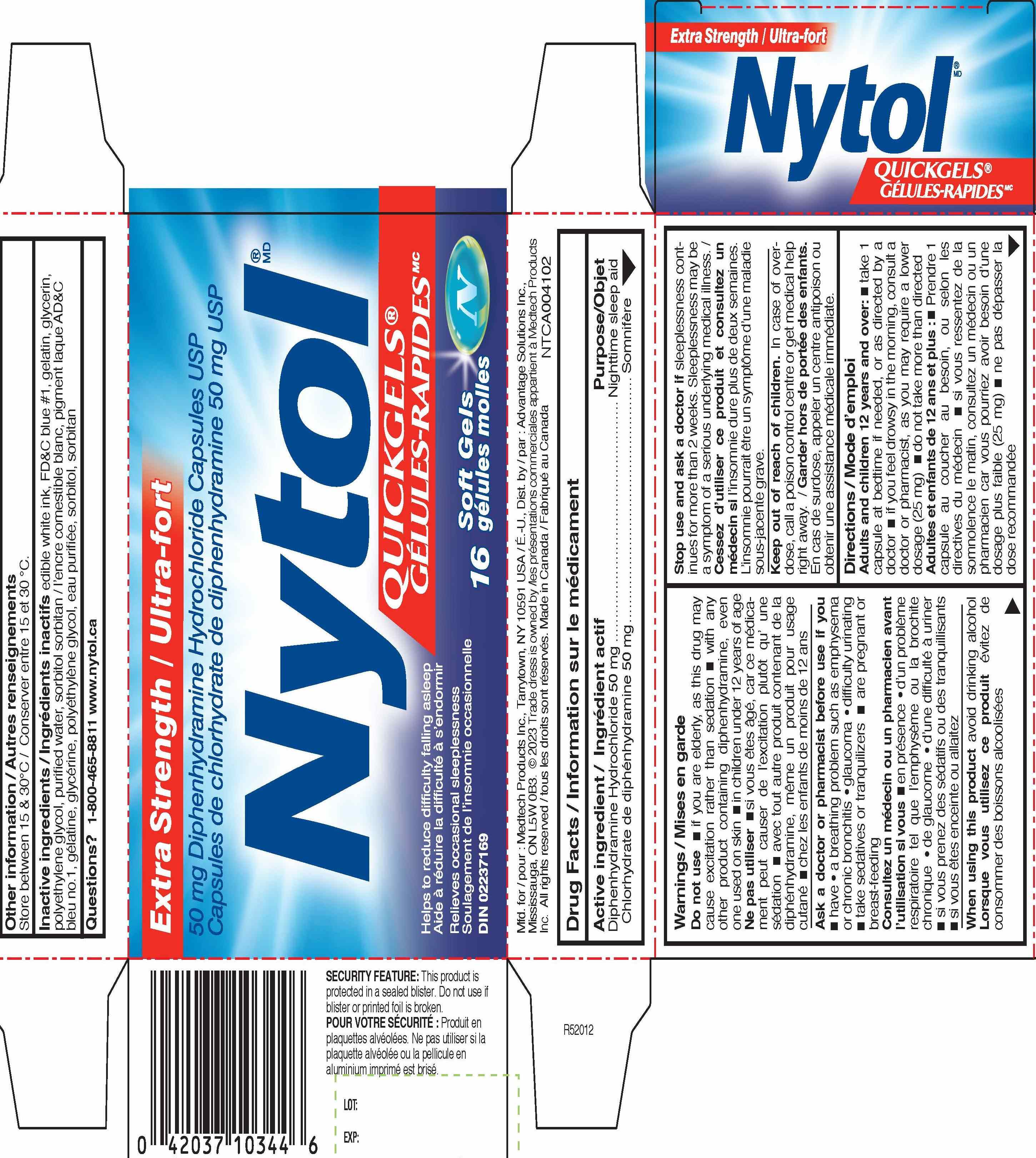 DRUG LABEL: Diphenhydramine Hydrochloride
NDC: 10267-5218 | Form: CAPSULE, LIQUID FILLED
Manufacturer: Contract Pharmacal Corp.
Category: otc | Type: HUMAN OTC DRUG LABEL
Date: 20240506

ACTIVE INGREDIENTS: DIPHENHYDRAMINE HYDROCHLORIDE 50 mg/1 1
INACTIVE INGREDIENTS: SORBITOL; GELATIN; GLYCERIN; WATER; FD&C BLUE NO. 1; POLYETHYLENE GLYCOL 400; SORBITAN

5218- Export